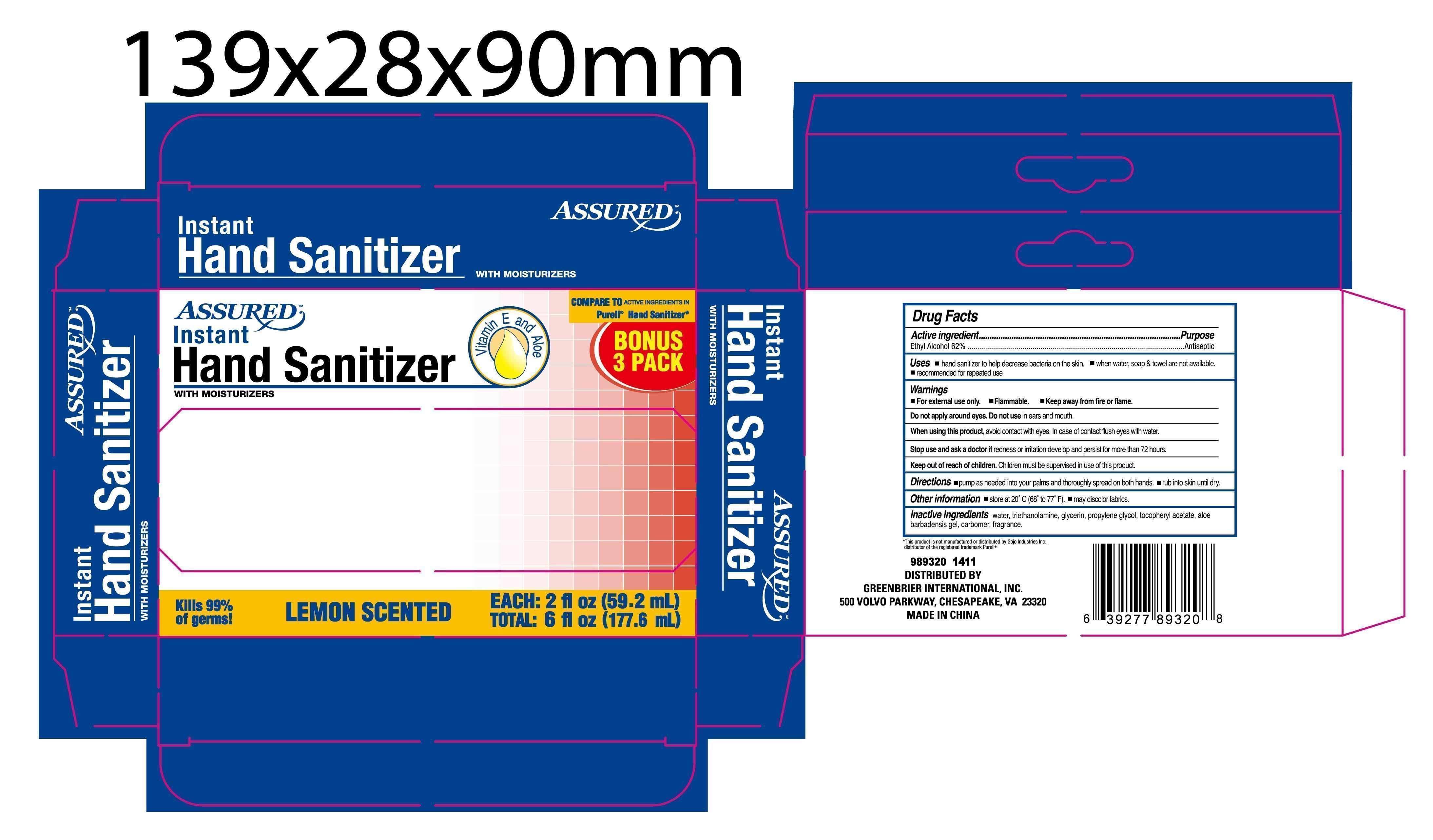 DRUG LABEL: 2 Pack Assured Instant Hand Sanitizer with moisturizers (Vitamin E and aloe)
NDC: 40104-201 | Form: GEL
Manufacturer: Ningbo Pulisi Daily Chemical Products Co., Ltd.
Category: otc | Type: HUMAN OTC DRUG LABEL
Date: 20141102

ACTIVE INGREDIENTS: alcohol 62 mL/100 mL
INACTIVE INGREDIENTS: WATER; PROPYLENE GLYCOL; ALOE VERA LEAF; CARBOMER 934; GLYCERIN; .ALPHA.-TOCOPHEROL ACETATE, D-

Drug facts

Active ingredient Purpose

Alcohol 62% ... Antiseptic

PURPOSE

Decreases bacteria on hands

KEEP OUT OF REACH OF CHILDREN

If swallowed, get medical help or contact local poison control center right away.

INDICATIONS AND USAGE

keep out of eyes

WARNINGS

For external use only.
Flammable. Keep away from hear or flame.
Stop using and ask a doctor, if irritation and redness develops, if condition persists for more than 72 hours, consult a doctor.

DOSAGE AND ADMINISTRATION

Place a "palmful" of product in one hand, spread on both hands and rub the skin until dry.

INACTIVE INGREDIENT

Water, Carbomer, Glycerin, Propylene Glycol, Triethanolamine, Aloe Barbadensis Leaf Juice, Tocopheryl Acetate, Fragrance